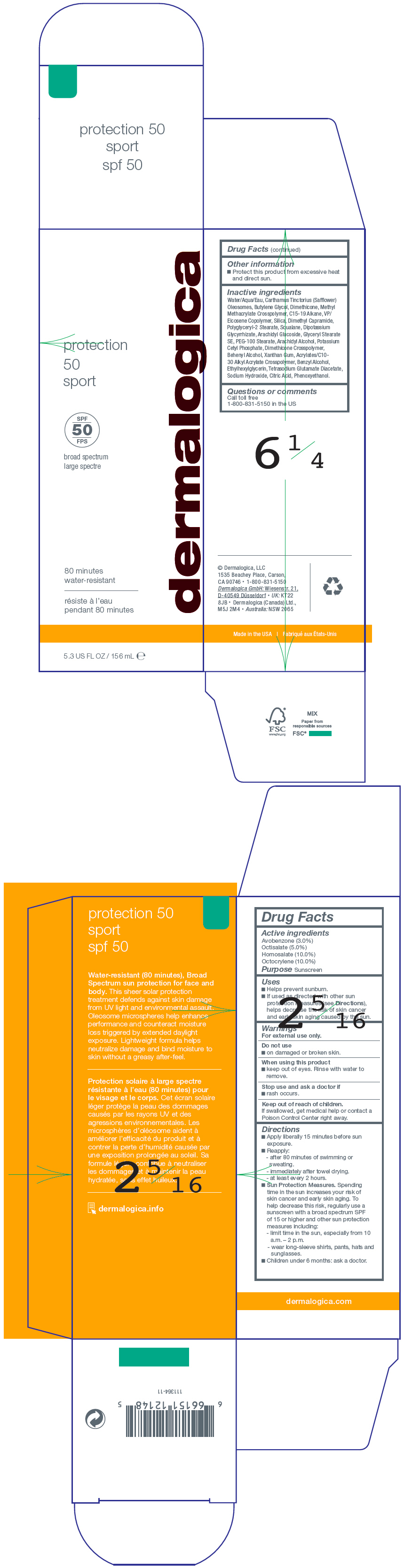 DRUG LABEL: Protection 50 Sport
NDC: 68479-232 | Form: LOTION
Manufacturer: Dermalogica, LLC.
Category: otc | Type: HUMAN OTC DRUG LABEL
Date: 20241230

ACTIVE INGREDIENTS: Homosalate 10 mg/100 mL; Octocrylene 10 mg/100 mL; Octisalate 5 mg/100 mL; Avobenzone 3 mg/100 mL
INACTIVE INGREDIENTS: Water; Butylene Glycol; SAFFLOWER OIL; Dimethicone; METHYL METHACRYLATE/GLYCOL DIMETHACRYLATE CROSSPOLYMER; C15-19 Alkane; VINYLPYRROLIDONE/EICOSENE COPOLYMER; SILICON DIOXIDE; Dimethyl Capramide; Polyglyceryl-2 Stearate; Phenoxyethanol; PEG-100 Stearate; Glyceryl Stearate SE; Arachidyl Alcohol; Potassium Cetyl Phosphate; Squalane; DOCOSANOL; Xanthan Gum; CARBOMER INTERPOLYMER TYPE A (ALLYL SUCROSE CROSSLINKED); Arachidyl Glucoside; Benzyl Alcohol; GLYCYRRHIZINATE DIPOTASSIUM; Ethylhexylglycerin; Tetrasodium Glutamate Diacetate; Sodium Hydroxide; ANHYDROUS CITRIC ACID

Protection 50 Sport

Drug Facts

Active ingredients

Avobenzone (3.0%)
Octisalate (5.0%)
Homosalate (10.0%)
Octocrylene (10.0%)

Purpose

Sunscreen

Uses

- Helps prevent sunburn.
- If used as directed with other sun protection measures (see Directions), helps decrease the risk of skin cancer and early skin aging caused by the sun.

Warnings

For external use only.

Do not use

- on damaged or broken skin.

When using this product

- keep out of eyes. Rinse with water to remove.

Stop use and ask a doctor if

- rash occurs.

Keep out of reach of children.

If swallowed, get medical help or contact a Poison Control Center right away.

Directions

- Apply liberally 15 minutes before sun exposure.
- Reapply:
  - after 80 minutes of swimming or sweating.
  - immediately after towel drying.
  - at least every 2 hours.
- Sun Protection Measures. Spending time in the sun increases your risk of skin cancer and early skin aging. To help decrease this risk, regularly use a sunscreen with a broad spectrum SPF of 15 or higher and other sun protection measures including:
  - limit time in the sun, especially from 10 a.m. – 2 p.m.
  - wear long-sleeve shirts, pants, hats and sunglasses.
- Children under 6 months: ask a doctor.

Other information

- Protect this product from excessive heat and direct sun.

Inactive ingredients

Water/Aqua/Eau, Carthamus Tinctorius (Safflower) Oleosomes, Butylene Glycol, Dimethicone, Methyl Methacrylate Crosspolymer, C15-19 Alkane, VP/ Eicosene Copolymer, Silica, Dimethyl Capramide, Polyglyceryl-2 Stearate, Squalane, Dipotassium Glycyrrhizate, Arachidyl Glucoside, Glyceryl Stearate SE, PEG-100 Stearate, Arachidyl Alcohol, Potassium Cetyl Phosphate, Dimethicone Crosspolymer, Behenyl Alcohol, Xanthan Gum, Acrylates/C10- 30 Alkyl Acrylate Crosspolymer, Benzyl Alcohol, Ethylhexylglycerin, Tetrasodium Glutamate Diacetate, Sodium Hydroxide, Citric Acid, Phenoxyethanol.

Questions or comments

Call toll free 1-800-831-5150 in the US

PRINCIPAL DISPLAY PANEL - 156 mL Tube Carton

protection
50
sport

SPF
50

broad spectrum

80 minutes
water-resistant

5.3 US FL OZ / 156 mL ℮

dermalogica